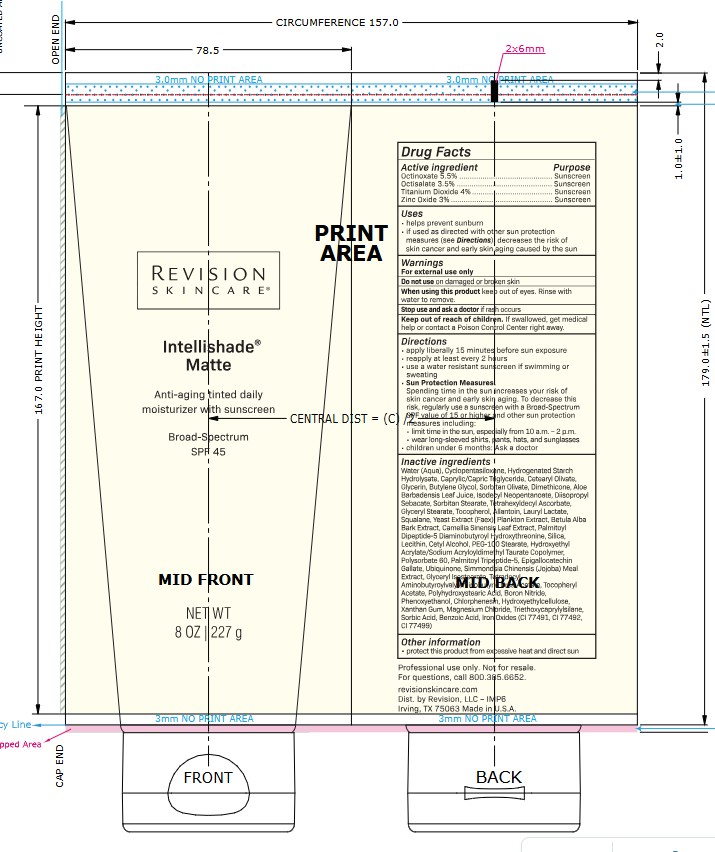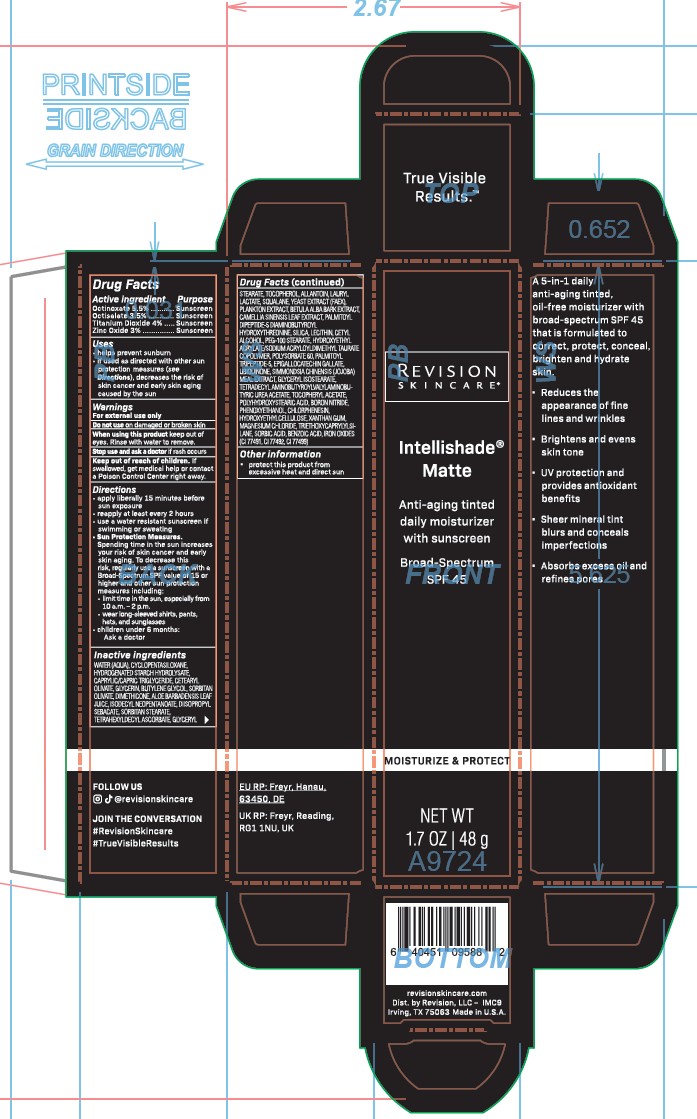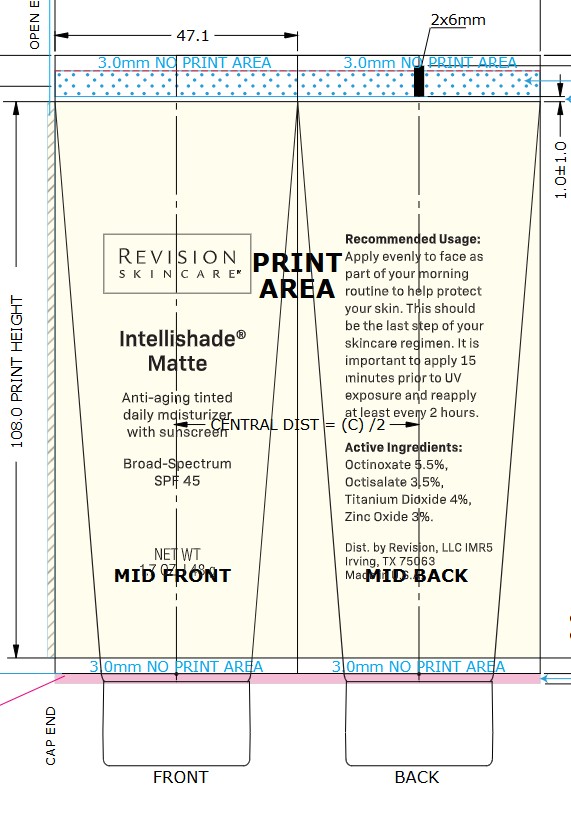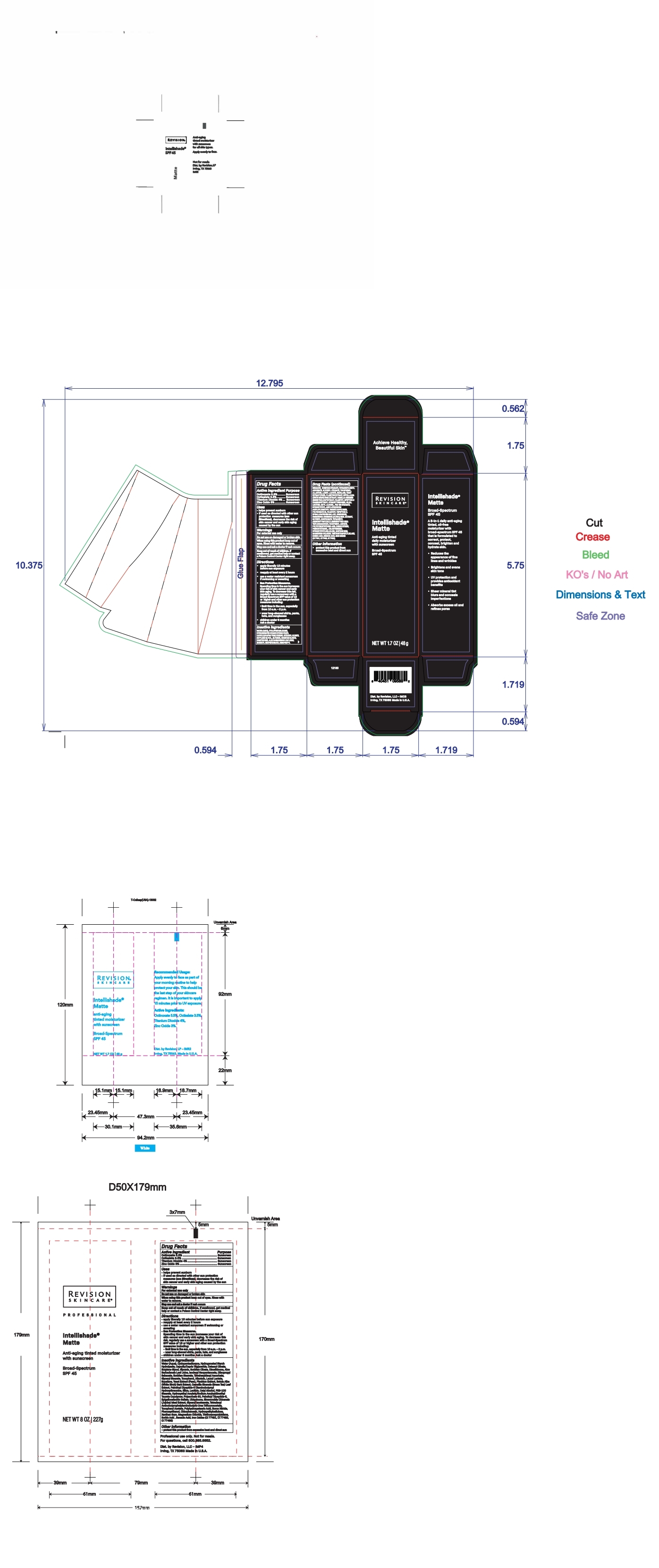 DRUG LABEL: Intellishade Matte SPF 45
NDC: 64651-7603 | Form: CREAM
Manufacturer: Revision, LLC
Category: otc | Type: HUMAN OTC DRUG LABEL
Date: 20260113

ACTIVE INGREDIENTS: OCTINOXATE 5.5 g/100 g; OCTISALATE 3.5 g/100 g; TITANIUM DIOXIDE 4 g/100 g; ZINC OXIDE 3 g/100 g
INACTIVE INGREDIENTS: WATER; CYCLOMETHICONE 5; MEDIUM-CHAIN TRIGLYCERIDES; CETEARYL OLIVATE; SORBITOL; GLYCERIN; SORBITAN OLIVATE; BUTYLENE GLYCOL; DIMETHICONE; ALOE VERA LEAF; ISODECYL NEOPENTANOATE; DIISOPROPYL SEBACATE; SORBITAN MONOSTEARATE; TETRAHEXYLDECYL ASCORBATE; GLYCERYL MONOSTEARATE; TOCOPHEROL; ALLANTOIN; LAURYL LACTATE; SQUALANE; YEAST; BETULA PUBESCENS BARK; SILICON DIOXIDE; LECITHIN, SOYBEAN; CETYL ALCOHOL; PEG-100 STEARATE; HYDROXYETHYL ACRYLATE/SODIUM ACRYLOYLDIMETHYL TAURATE COPOLYMER (45000 MPA.S AT 1%); POLYSORBATE 60; PALMITOYL TRIPEPTIDE-5; EPIGALLOCATECHIN GALLATE; UBIDECARENONE; SIMMONDSIA CHINENSIS SEED; GLYCERYL ISOSTEARATE; .ALPHA.-TOCOPHEROL ACETATE; POLYHYDROXYSTEARIC ACID (2300 MW); BORON NITRIDE; PHENOXYETHANOL; CHLORPHENESIN; HYDROXYETHYL CELLULOSE (2000 CPS AT 1%); XANTHAN GUM; MAGNESIUM CHLORIDE; TRIETHOXYCAPRYLYLSILANE; SORBIC ACID; BENZOIC ACID; FERRIC OXIDE RED

Intellishade Matte SPF 45

1.7oz Revision Intellishade® Matte

ITM_retail_carton_IMC5

ITM_retail_tube_IMR5

Intellishade®
Matte

anti-aging
tinted moisturizer
with sunscreen

Broad-Spectrum
SPF 45

NET WT 1.7 OZ | 48 g

Active ingredient ........ Purpose

Octinoxate 5.5% ........... Sunscreen
Octisalate 3.5% ............. Sunscreen
Titanium Dioxide 4% ...... Sunscreen
Zinc Oxide 3% .............. Sunscreen

Uses

• helps prevent sunburn
• if used as directed with other sun protection measures (see Directions),
decreases the risk of skin cancer and early skin aging caused by the sun

Warnings

For external use only

Do not useon damaged or broken skin

WHEN USING

When using this productkeep out of eyes. Rinse with water to remove.

Stop use and ask a doctorif rash occurs

Keep out of reach of children.If swallowed, get medical help or contact a Poison Control Center right away.

Directions

• apply liberally 15 minutes before sun exposure
• reapply at least every 2 hours
• use a water resistant sunscreen if swimming or sweating
• Sun Protection Measures.
Spending time in the sun increases your risk of skin cancer and early skin aging. To decrease this risk, regularly
use a sunscreen with a Broad-Spectrum SPF value of 15 or higher and other sun protection measures including:
• limit time in the sun, especially from 10 a.m. – 2 p.m.
• wear long-sleeved shirts, pants, hats, and sunglasses
• children under 6 months:
Ask a doctor

Inactive ingredients

Water (Aqua), Cyclopentasiloxane, Hydrogenated Starch Hydrolysate, Caprylic/Capric Triglyceride, Cetearyl Olivate, Glycerin, Butylene Glycol, Sorbitan Olivate, Dimethicone, Aloe Barbadensis Leaf Juice, Isodecyl Neopentanoate, Diisopropyl Sebacate, Sorbitan Stearate, Tetrahexyldecyl Ascorbate, Glyceryl Stearate, Tocopherol, Allantoin, Lauryl Lactate, Squalane, Yeast Extract (Faex), Plankton Extract, Betula Alba Bark Extract, Camellia Sinensis Leaf Extract, Palmitoyl Dipeptide-5 Diaminobutyroyl Hydroxythreonine, Silica, Lecithin, Cetyl Alcohol, PEG-100 Stearate, Hydroxyethyl Acrylate/Sodium Acryloyldimethyl Taurate Copolymer, Polysorbate 60, Palmitoyl Tripeptide-5, Epigallocatechin Gallate, Ubiquinone, Simmondsia Chinensis (Jojoba) Meal Extract, Glyceryl Isostearate, Tetradecyl Aminobutyroylvalylaminobutyric Urea Acetate, Tocopheryl Acetate, Polyhydroxystearic Acid, Boron Nitride, Phenoxyethanol, Chlorphenesin, Hydroxyethylcellulose, Xanthan Gum, Magnesium Chloride, Triethoxycaprylylsilane, Sorbic Acid, Benzoic Acid, Iron Oxides (CI 77491, CI 77492, CI 77499)

Other information

• protect this product from excessive heat and direct sun

Dist. by Revision, LP
Irving, TX 75063 Made in U.S.A.

8oz Revision Intellishade® Matte

ITM_pro_tube_IMP6

PROFESSIONAL

Intellishade®
Matte

anti-aging
tinted moisturizer
with sunscreen

Broad-Spectrum
SPF 45

NET WT 8 OZ | 227 g

Active ingredient ........ Purpose

Octinoxate 5.5% ........... Sunscreen
Octisalate 3.5% ............. Sunscreen
Titanium Dioxide 4% ...... Sunscreen
Zinc Oxide 3% .............. Sunscreen

Uses

• helps prevent sunburn
• if used as directed with other sun protection measures (see Directions),
decreases the risk of skin cancer and early skin aging caused by the sun

Warnings

For external use only

Do not useon damaged or broken skin

WHEN USING

When using this productkeep out of eyes. Rinse with water to remove.

Stop use and ask a doctorif rash occurs

Keep out of reach of children.If swallowed, get medical help or contact a Poison Control Center right away.

Directions

• apply liberally 15 minutes before sun exposure
• reapply at least every 2 hours
• use a water resistant sunscreen if swimming or sweating
• Sun Protection Measures.
Spending time in the sun increases your risk of skin cancer and early skin aging. To decrease this risk, regularly
use a sunscreen with a Broad-Spectrum SPF value of 15 or higher and other sun protection measures including:
• limit time in the sun, especially from 10 a.m. – 2 p.m.
• wear long-sleeved shirts, pants, hats, and sunglasses
• children under 6 months:
Ask a doctor

Inactive ingredients

Water (Aqua), Cyclopentasiloxane, Hydrogenated Starch Hydrolysate, Caprylic/Capric Triglyceride, Cetearyl Olivate, Glycerin, Butylene Glycol, Sorbitan Olivate, Dimethicone, Aloe Barbadensis Leaf Juice, Isodecyl Neopentanoate, Diisopropyl Sebacate, Sorbitan Stearate, Tetrahexyldecyl Ascorbate, Glyceryl Stearate, Tocopherol, Allantoin, Lauryl Lactate, Squalane, Yeast Extract (Faex), Plankton Extract, Betula Alba Bark Extract, Camellia Sinensis Leaf Extract, Palmitoyl Dipeptide-5 Diaminobutyroyl Hydroxythreonine, Silica, Lecithin, Cetyl Alcohol, PEG-100 Stearate, Hydroxyethyl Acrylate/Sodium Acryloyldimethyl Taurate Copolymer, Polysorbate 60, Palmitoyl Tripeptide-5, Epigallocatechin Gallate, Ubiquinone, Simmondsia Chinensis (Jojoba) Meal Extract, Glyceryl Isostearate, Tetradecyl Aminobutyroylvalylaminobutyric Urea Acetate, Tocopheryl Acetate, Polyhydroxystearic Acid, Boron Nitride, Phenoxyethanol, Chlorphenesin, Hydroxyethylcellulose, Xanthan Gum, Magnesium Chloride, Triethoxycaprylylsilane, Sorbic Acid, Benzoic Acid, Iron Oxides (CI 77491, CI 77492, CI 77499)

Other information

• protect this product from excessive heat and direct sun

Dist. by Revision, LP
Irving, TX 75063 Made in U.S.A.

DOSAGE AND ADMINISTRATION

apply liberally 15 minutes before sun exposure
reapply at least every two hours
use a water resistant sunscreen if swimming or sweating

PURPOSE

Anti-aging tinted daily moisturizer with sunscreen

Broad Spectrum

SPF 45